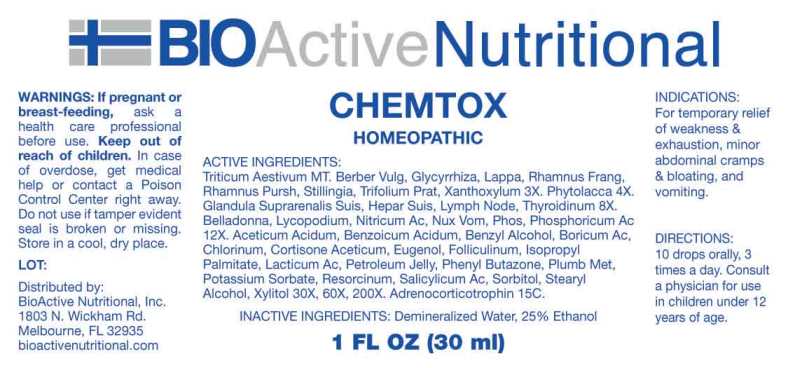 DRUG LABEL: Chemtox
NDC: 43857-0654 | Form: LIQUID
Manufacturer: BioActive Nutritional, Inc.
Category: homeopathic | Type: HUMAN OTC DRUG LABEL
Date: 20250107

ACTIVE INGREDIENTS: TRITICUM AESTIVUM WHOLE 1 [hp_X]/1 mL; BERBERIS VULGARIS ROOT BARK 3 [hp_X]/1 mL; GLYCYRRHIZA GLABRA 3 [hp_X]/1 mL; ARCTIUM LAPPA ROOT 3 [hp_X]/1 mL; FRANGULA ALNUS BARK 3 [hp_X]/1 mL; FRANGULA PURSHIANA BARK 3 [hp_X]/1 mL; STILLINGIA SYLVATICA ROOT 3 [hp_X]/1 mL; TRIFOLIUM PRATENSE FLOWER 3 [hp_X]/1 mL; ZANTHOXYLUM AMERICANUM BARK 3 [hp_X]/1 mL; PHYTOLACCA AMERICANA ROOT 4 [hp_X]/1 mL; SUS SCROFA ADRENAL GLAND 8 [hp_X]/1 mL; PORK LIVER 8 [hp_X]/1 mL; SUS SCROFA LYMPH 8 [hp_X]/1 mL; THYROID 8 [hp_X]/1 mL; ATROPA BELLADONNA 12 [hp_X]/1 mL; LYCOPODIUM CLAVATUM SPORE 12 [hp_X]/1 mL; NITRIC ACID 12 [hp_X]/1 mL; STRYCHNOS NUX-VOMICA SEED 12 [hp_X]/1 mL; PHOSPHORIC ACID 12 [hp_X]/1 mL; PHOSPHORUS 12 [hp_X]/1 mL; SALICYLIC ACID 30 [hp_X]/1 mL; CORTISONE ACETATE 30 [hp_X]/1 mL; EUGENOL 30 [hp_X]/1 mL; STEARYL ALCOHOL 30 [hp_X]/1 mL; XYLITOL 30 [hp_X]/1 mL; ESTRONE 30 [hp_X]/1 mL; BENZOIC ACID 30 [hp_X]/1 mL; CHLORINE 30 [hp_X]/1 mL; POTASSIUM SORBATE 30 [hp_X]/1 mL; SORBITOL 30 [hp_X]/1 mL; RESORCINOL 30 [hp_X]/1 mL; BENZYL ALCOHOL 30 [hp_X]/1 mL; LACTIC ACID, DL- 30 [hp_X]/1 mL; ISOPROPYL PALMITATE 30 [hp_X]/1 mL; BORIC ACID 30 [hp_X]/1 mL; ACETIC ACID 30 [hp_X]/1 mL; PHENYLBUTAZONE 30 [hp_X]/1 mL; PETROLATUM 30 [hp_X]/1 mL; LEAD 30 [hp_X]/1 mL; CORTICOTROPIN 15 [hp_C]/1 mL
INACTIVE INGREDIENTS: WATER; ALCOHOL

DRUG FACTS:

ACTIVE INGREDIENTS:

Triticum Aestivum MT, Berberis Vulgaris 3X, Glycyrrhiza Glabra 3X, Lappa Major 3X, Rhamnus Frangula 3X, Rhamnus Purshiana 3X, Stillingia Sylvatica 3X, Trifolium Pratense 3X, Xanthoxylum Fraxineum 3X, Phytolacca Decandra 4X, Glandula Suprarenalis Suis 8X, Hepar Suis 8X, Lymph Node 8X, Thyroidinum 8X, Belladonna 12X, Lycopodium Clavatum 12X, Nitricum Acidum 12X, Nux Vomica 12X, Phosphoricum Acidum 12X, Phosphorus 12X, Salicylicum Acidum 30X, 60X, 200X, Cortisone Aceticum 30X, 60X, 200X, Eugenol 30X, 60X, 200X, Stearyl Alcohol 30X, 60X, 200X, Xylitol 30X, 60X, 200X, Folliculinum 30X, 60X, 200X, Benzoicum Acidum 30X, 60X, 200X, Chlorinum 30X, 60X, 200X, Potassium Sorbate 30X, 60X, 200X, Sorbitol 30X, 60X, 200X, Resorcinum 30X, 60X, 200X, Benzyl Alcohol 30X, 60X, 200X, Lacticum Acidum 30X, 60X, 200X, Isopropyl Palmitate 30X, 60X, 200X, Boricum Acidum 30X, 60X, 200X, Aceticum Acidum 30X, 60X, 200X, Phenyl Butazone 30X, 60X, 200X, Petroleum Jelly 30X, 60X, 200X, Plumbum Metallicum 30X, 60X, 200X, Adrenocorticotrophin 15C.

PURPOSE:

For temporary relief of weakness & exhaustion, minor abdominal cramps & bloating, and vomiting.

WARNINGS:

If pregnant or breast-feeding, ask a health care professional before use.

Keep out of reach of children. In case of overdose, get medical help or contact a Poison Control Center right away.

Do not use if tamper evident seal is broken or missing.

Store in a cool, dry place.

KEEP OUT OF REACH OF CHILDREN:

In case of overdose, get medical help or contact a Poison Control Center right away.

DIRECTIONS:

10 drops orally, 3 times a day. Consult a physician for use in children under 12 years of age.

INDICATIONS:

For temporary relief of weakness & exhaustion, minor abdominal cramps & bloating, and vomiting.

INACTIVE INGREDIENTS:

Demineralized Water, 25% Ethanol

QUESTIONS:

Distributed by:
BioActive Nutritional, Inc.
1803 N. Wickham Rd.
Melbourne, FL 32935
bioactivenutritional.com

PACKAGE LABEL DISPLAY:

BIOActiveNutritional

CHEMTOX

HOMEOPATHIC

1 FL OZ (30 ml)